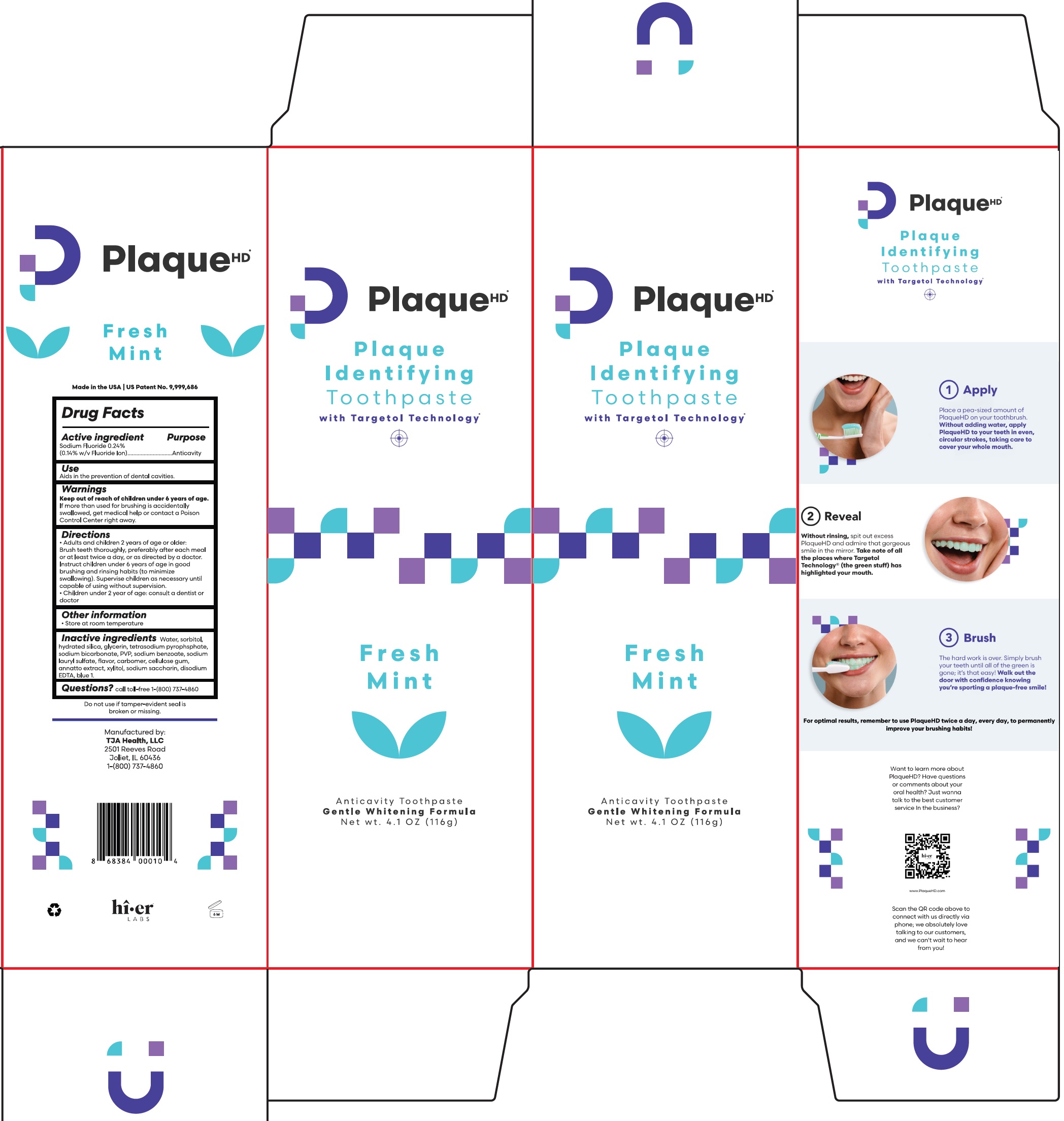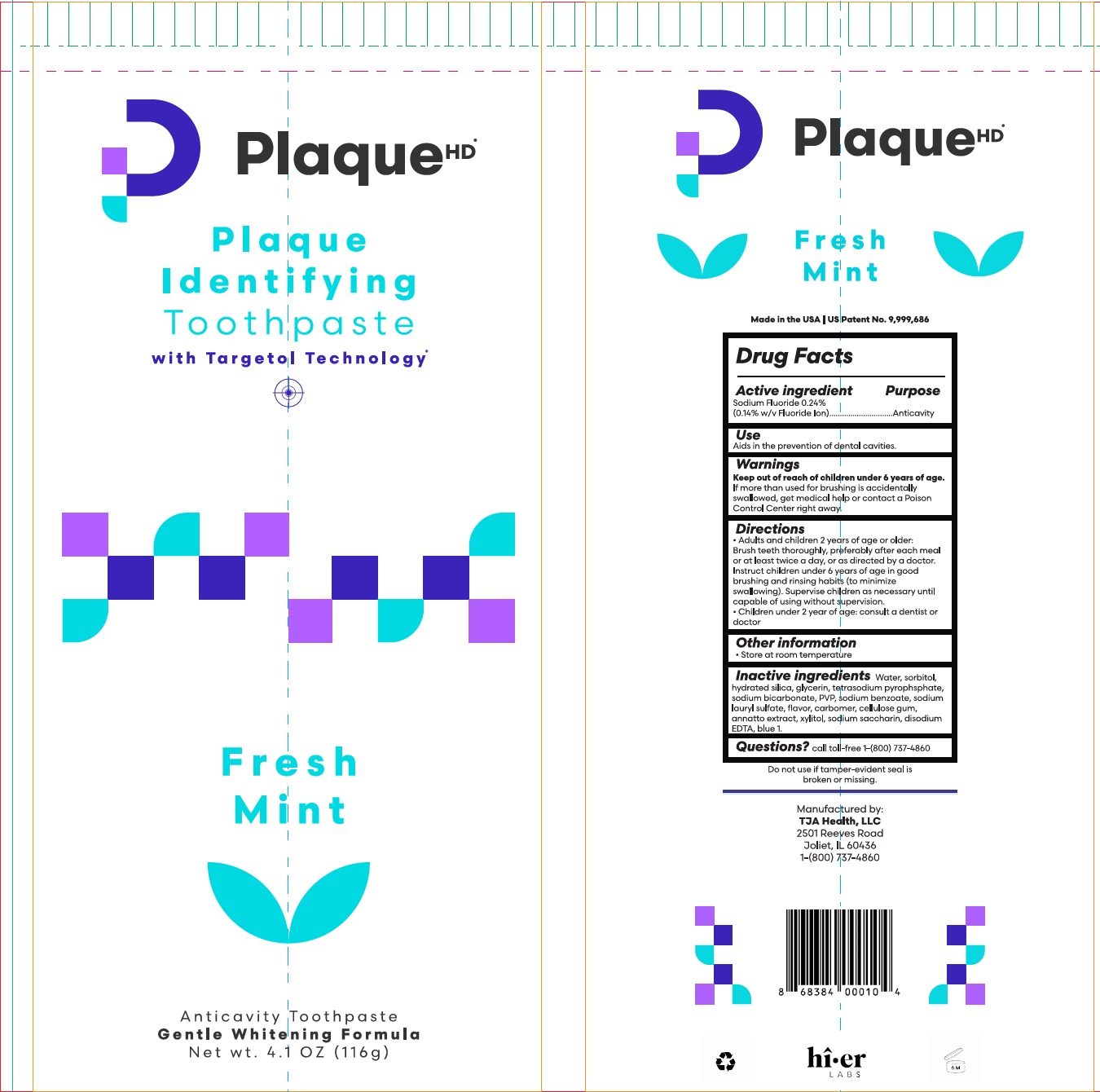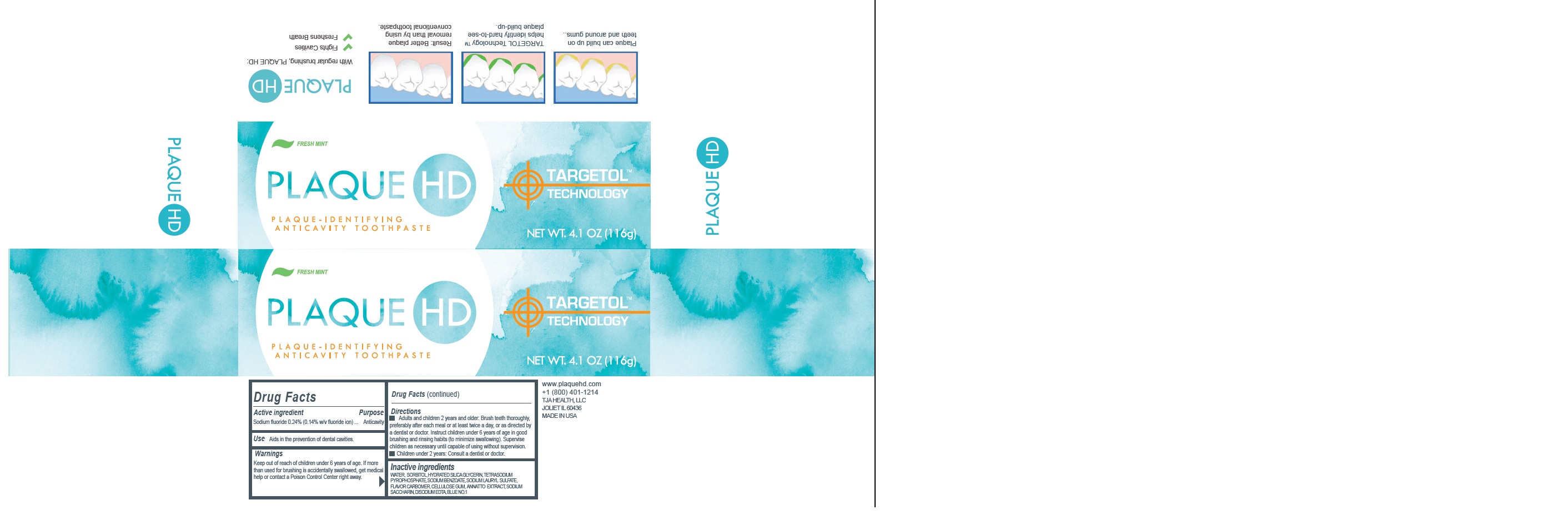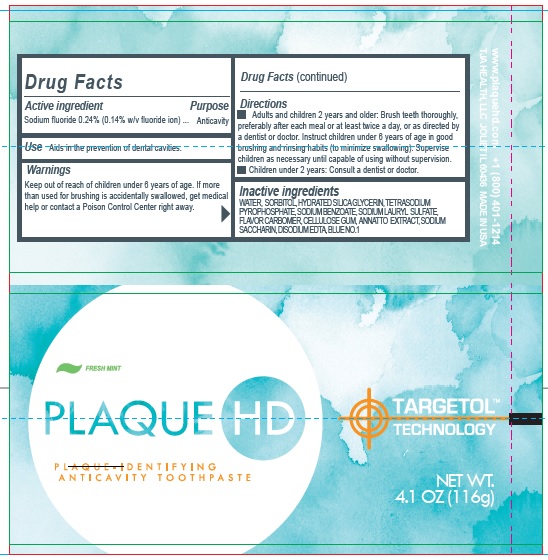 DRUG LABEL: PLAQUE HD ANTICAVITY FRESH MINT FLAVOR
NDC: 57660-000 | Form: PASTE, DENTIFRICE
Manufacturer: TJA Health LLC
Category: otc | Type: HUMAN OTC DRUG LABEL
Date: 20250529

ACTIVE INGREDIENTS: SODIUM FLUORIDE 0.14 g/100 g
INACTIVE INGREDIENTS: WATER; SORBITOL; HYDRATED SILICA; GLYCERIN; SODIUM PYROPHOSPHATE; SODIUM BICARBONATE; POVIDONE, UNSPECIFIED; SODIUM BENZOATE; SODIUM LAURYL SULFATE; CARBOMER HOMOPOLYMER, UNSPECIFIED TYPE; CARBOXYMETHYLCELLULOSE SODIUM, UNSPECIFIED; ANNATTO; XYLITOL; SACCHARIN SODIUM; EDETATE DISODIUM; FD&C BLUE NO. 1

PLAQUE HD ANTICAVITY TOOTHPASTE FRESH MINT FLAVOR

Active Ingredient

Sodium Fluoride 0.24% (0.14% w/v Fluoride Ion)

Purpose

Anticavity

Use

Aids in the prevention of dental cavities.

Warnings

Keep out of reach of children

under 6 years of age. If more than used for brushing is accidentally swallowed, get medical help or contact a Poison Control Center right away.

Directions

- Adults and children 2 years of age or older: Brush teeth thoroughly, preferably after each meal or at least twice a day, or as directed by a doctor. Instruct children under 6 years of age in good brushing and rinsing habits (to minimize swallowing). Supervise children as necessary until capable of using without supervision.
- Children under 2 year of age: Consult a dentist or doctor

Other information

- Store at room temperature

Inactive ingredients

Water, sorbitol, hydrated silica, glycerin, tetrasodium pyrophsphate, sodium bicarbonate, PVP, sodium benzoate, sodium lauryl sulfate, flavor, carbomer, cellulose gum, annatto extract, xylitol, sodium saccharin, disodium EDTA, blue 1.

Questions?

call toll-free-1-(800) 737-4860